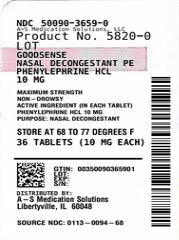 DRUG LABEL: Good Sense Nasal Decongestant PE
NDC: 50090-3659 | Form: TABLET
Manufacturer: A-S Medication Solutions
Category: otc | Type: HUMAN OTC DRUG LABEL
Date: 20240625

ACTIVE INGREDIENTS: PHENYLEPHRINE HYDROCHLORIDE 10 mg/1 1
INACTIVE INGREDIENTS: ANHYDROUS DIBASIC CALCIUM PHOSPHATE; CARNAUBA WAX; MAGNESIUM STEARATE; MICROCRYSTALLINE CELLULOSE; POLYETHYLENE GLYCOL, UNSPECIFIED; POLYVINYL ALCOHOL, UNSPECIFIED; SILICON DIOXIDE; TALC; TITANIUM DIOXIDE; FD&C RED NO. 40

Perrigo Nasal Decongestant PE Drug Facts

Active ingredient (in each tablet)

Phenylephrine hydrochloride 10 mg

Purpose

Nasal decongestant

Uses

- temporarily relieves sinus congestion and pressure
- temporarily relieves nasal congestion due to the common cold, hay fever or other upper respiratory allergies

Warnings

Do not use

if you are now taking a prescription monoamine oxidase inhibitor (MAOI) (certain drugs for depression, psychiatric or emotional conditions, or Parkinson’s disease), or for 2 weeks after stopping the MAOI drug. If you do not know if your prescription drug contains an MAOI, ask a doctor or pharmacist before taking this product.

Ask a doctor before use if you have

- heart disease
- high blood pressure
- thyroid disease
- diabetes
- trouble urinating due to an enlarged prostate gland

When using this product

do not exceed recommended dosage

Stop use and ask a doctor if

- nervousness, dizziness, or sleeplessness occur
- symptoms do not improve within 7 days or occur with a fever

If pregnant or breast-feeding,

ask a health professional before use.

Keep out of reach of children.

In case of overdose, get medical help or contact a Poison Control Center right away (1-800-222-1222).

Directions

adults and children 12 years and over | - take 1 tablet every 4 hours - do not take more than 6 tablets in 24 hours
children under 12 years | ask a doctor

Other information

- store at 20-25°C (68-77°F)
- do not use if blister unit is broken or torn

Inactive ingredients

anhydrous dibasic calcium phosphate, carnauba wax, FD&C red no. 40 aluminum lake, lecithin, magnesium stearate, microcrystalline cellulose, polyethylene glycol, polyvinyl alcohol, silicon dioxide, talc, titanium dioxide

Questions or comments?

1-800-719-9260